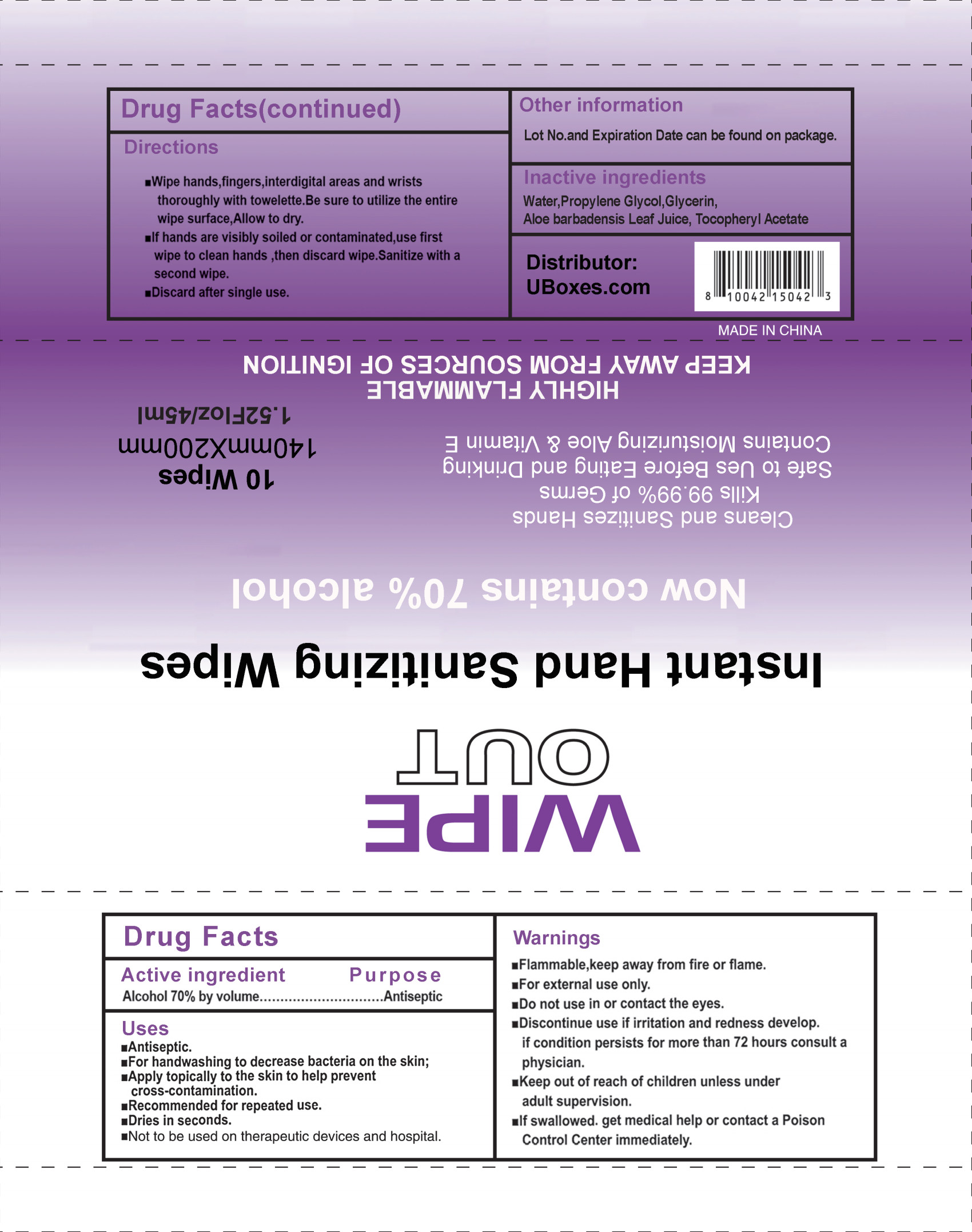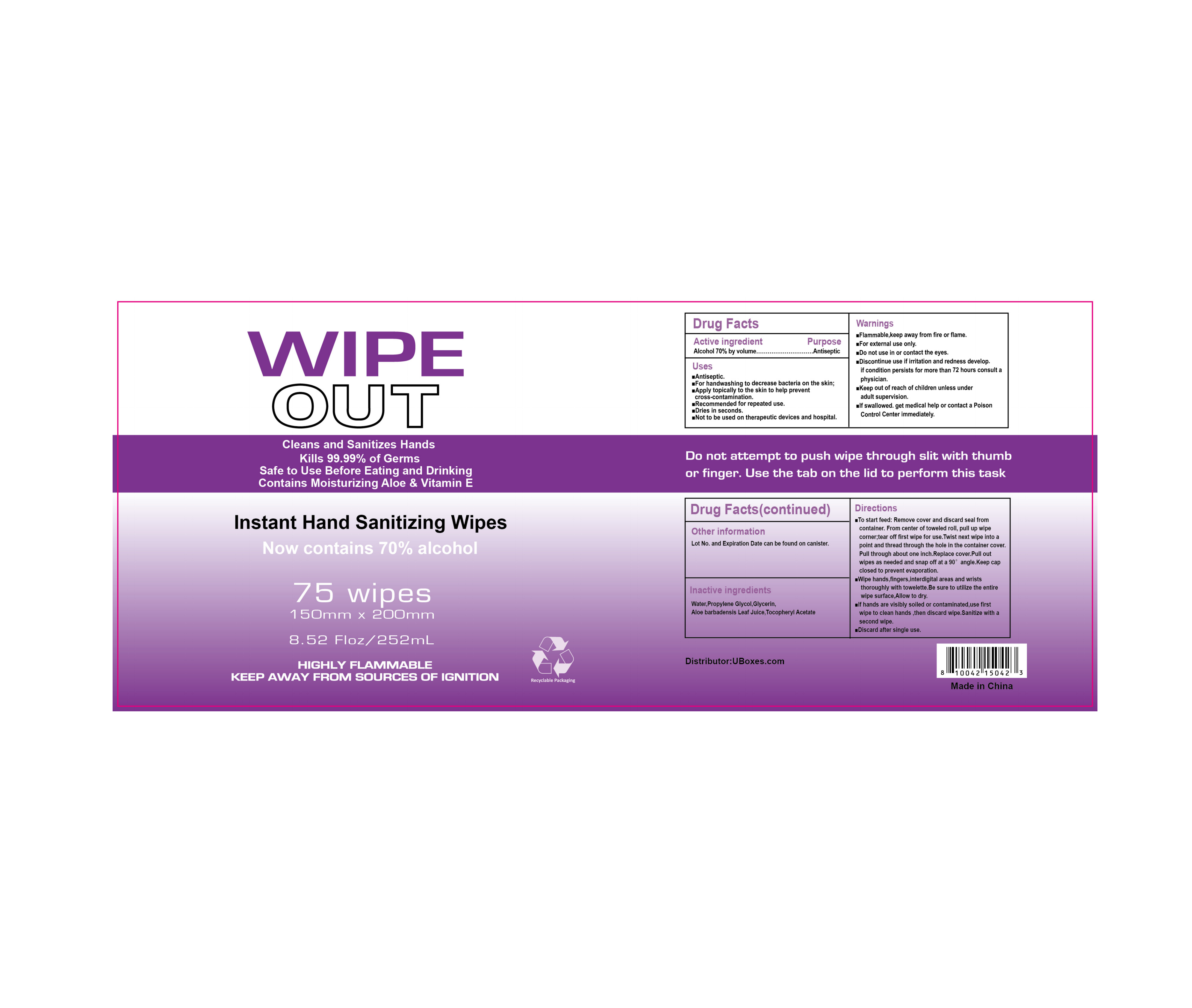 DRUG LABEL: Instant Hand sanitizing Wipes
NDC: 76991-006 | Form: CLOTH
Manufacturer: Hefei Wenqi Industrial & Trade Co., Ltd
Category: otc | Type: HUMAN OTC DRUG LABEL
Date: 20200513

ACTIVE INGREDIENTS: ALCOHOL 70 mL/100 mL
INACTIVE INGREDIENTS: GLYCERIN; PROPYLENE GLYCOL; WATER

Active Ingredient(s)

Alcohol 70% v/v. Purpose: Antiseptic

Purpose

Purpose: Antiseptic

Use

For hand washing to decrease bacteria on the skin;apply topically to the skin to help prevent cross-contamination Recommended for repeated use Dries in seconds a not to be used on therapeutic devices and hospital

Warnings

Flammable, keep away from fire or flameFor external use or Do not use in or contact the eyesDiscontinue use if irritation and redness developif condition persists for more than 72 hours consultphysician

Keep out of reach of children unless undeadult supervision

if swallowed. get medical help or contact a PoisonControl Center immediately

Do not use

- in children less than 2 months of age
- on open skin wounds

WHEN USING

Flammable, keep away from fire or flameFor external use orDo not use in or contact the eyesDiscontinue use if irritation and redness developif condition persists for more than 72 hours consultphysicianKeep out of reach of children unless undeadult supervisionaf swallowed. get medical help or contact a PoisonControl Center immediately

Do not use in or contact the eyes Discontinue use if irritation and redness developif condition persists for more than 72 hours consultphysicianKeep out of reach of children unless undeadult supervisionaf swallowed. get medical help or contact a PoisonControl Center immediately

Keep out of reach of children unless undeadult supervision

Directions

wipe hands, fingers, interdigital areas and wriststhoroughly with towelette. Be sure to utilize the entirewipe surface, Allow to dry.alf hands are visibly soiled or contaminated use firstwipe to clean hands, then discard wipe Sanitize with asecond wipendiscard after single use.

Other information

- Store between 15-30C (59-86F)
- Avoid freezing and excessive heat above 40C (104F)

Inactive ingredients

Water, Propylene Glycol, GlycerinAloe barbadensis Leaf Juice, Tocopheryl Acetate